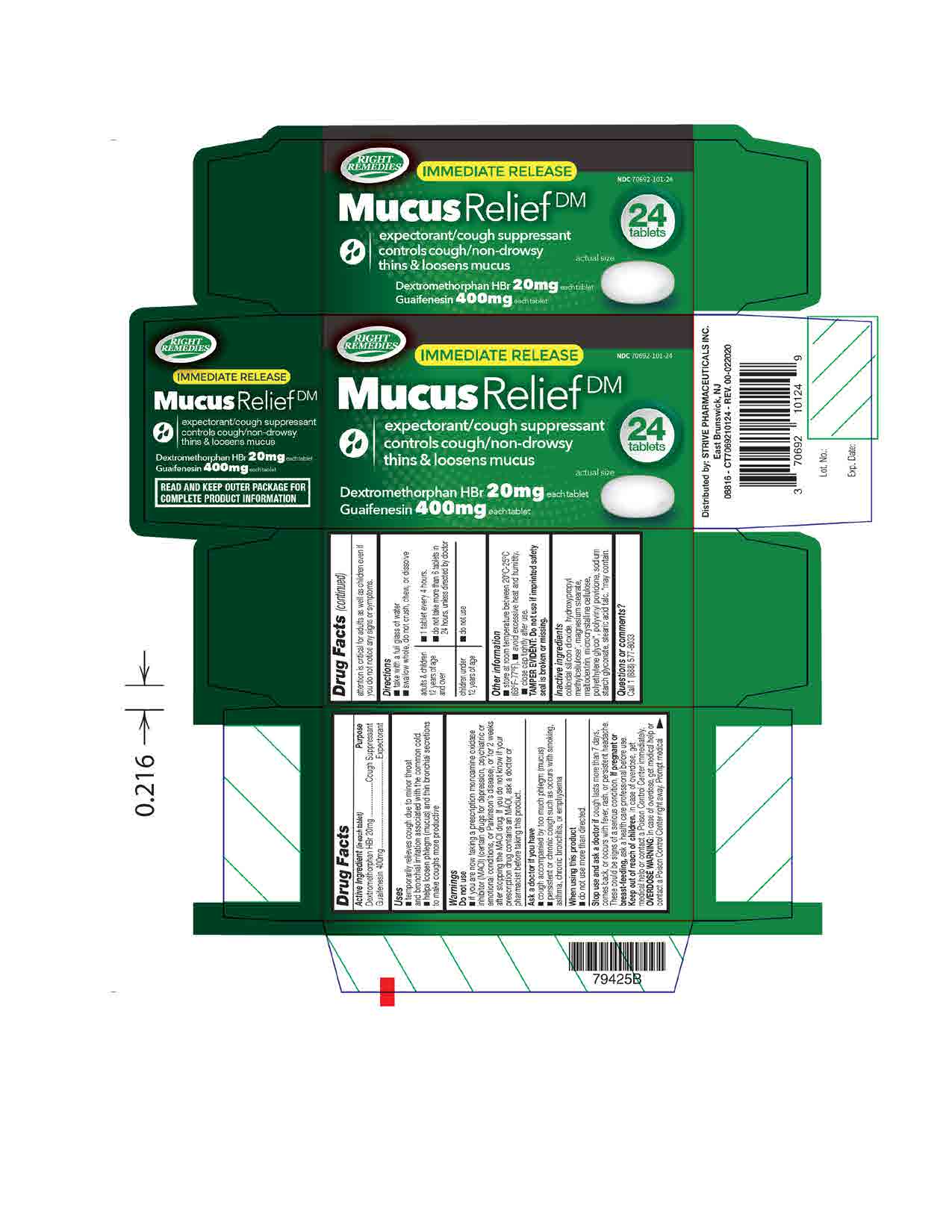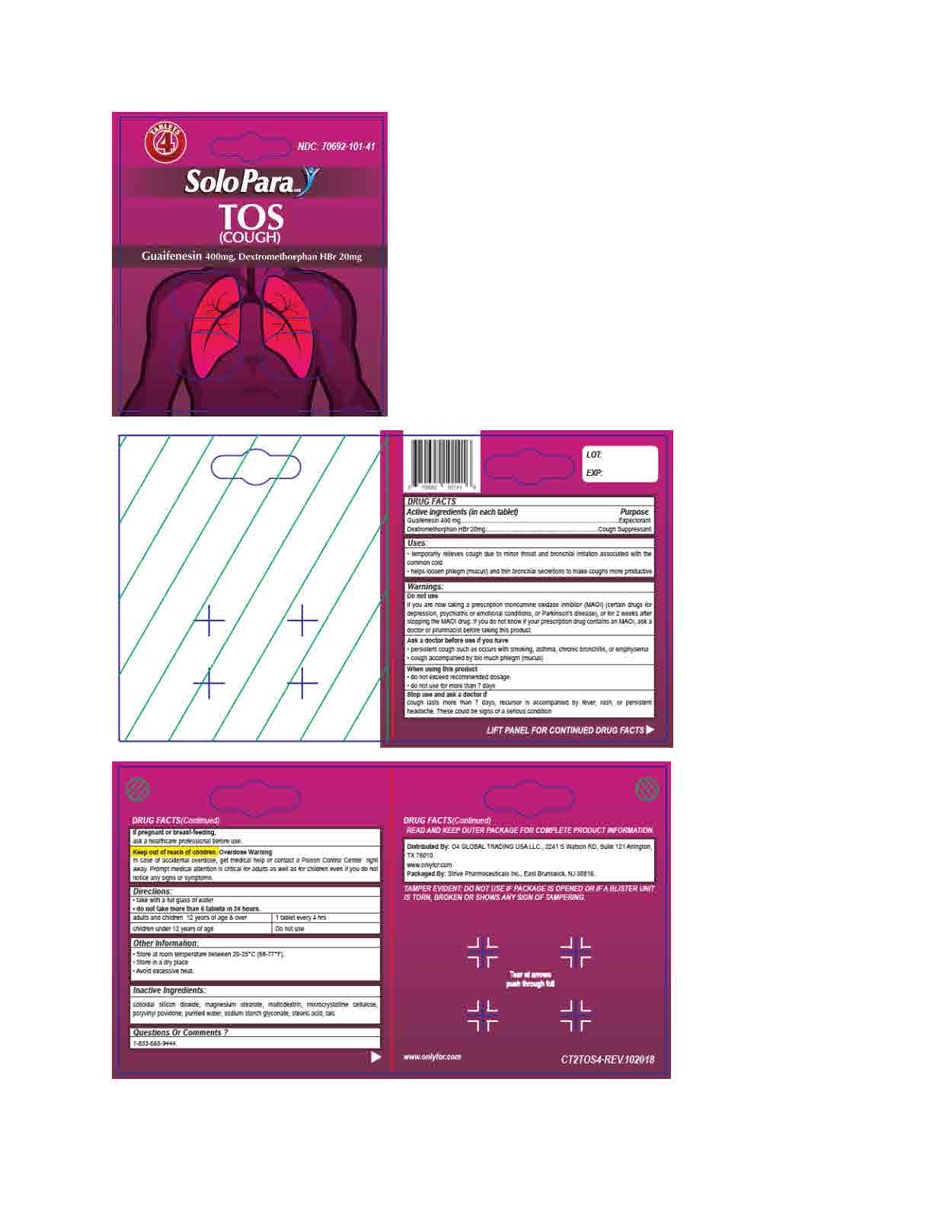 DRUG LABEL: Cough Mucus Relief DM
NDC: 70692-101 | Form: TABLET
Manufacturer: Strive Pharmaceuticals Inc.
Category: otc | Type: HUMAN OTC DRUG LABEL
Date: 20201013

ACTIVE INGREDIENTS: GUAIFENESIN 400 mg/1 1; DEXTROMETHORPHAN HYDROBROMIDE 20 mg/1 1
INACTIVE INGREDIENTS: HYPROMELLOSE, UNSPECIFIED; CELLULOSE, MICROCRYSTALLINE; SODIUM STARCH GLYCOLATE TYPE A CORN; TALC; SILICON DIOXIDE; MAGNESIUM STEARATE; POVIDONE, UNSPECIFIED; MALTODEXTRIN; STEARIC ACID; POLYETHYLENE GLYCOL 400

Dextromethorphan HBr 20mg and Guaifenesin 400mg

ACTIVE INGREDIENT

Dextromethorphan HBr 20mg

Guaifenesin 400mg

INACTIVE INGREDIENT

microcrystalline cellulose, sodium starch glycolate, talc, colloidal silicon dioxide,magnesium stearate, polyvinyl povidone, maltodextrin, stearic acid

* May contain hydroxypropyl methylcellulose, polyethylene glycol

DOSAGE AND ADMINISTRATION

* take with a full glass of water

* swallow whole; do not crush, chew or dissolve

*do not take more than 6 tablets in 24 hours

adults and children 12 years of age and over | 1 tablet every 4 hours
children under 12 years of age | Do not use

INDICATIONS AND USAGE

* temporarily relieves cough due to minor throat and bronchial irritation associated with the common cold

* helps loosen phlegm (mucus) and thin bronchial secretions to make coughs more productive

Do not use if you are now taking a prescription monoamine oxidase inhibitor (MAOI) (certain drugs for depression, psychiatric or emotional conditions, or Parkinson's disease), or for 2 weeks after stopping the MAOI drug. If you do not know if your prescription drug contains an MAOI, ask a doctor or pharmacist before taking this product.

Ask a doctor before use if you have

* persistent or chronic cough such as occurs with smoking, asthma, chronic bronchitis,or emphysema

* cough accompanied by too much phlegm (mucus)

When using this product do not use more than directed

Stop use and ask a doctor if cough lasts more than 7 days, comes back, or occurs with fever, rash, or persistent headache. These could be signs of a serious condition.

If pregnant or breast-feeding, ask a health professional before use.

Keep out of reach of children. In case of accidental overdose, get medical help or contact a Poison Control Center right away. Prompt medical attention is critical for adults as well as for children even if you do not notice any signs or symptoms.

KEEP OUT OF REACH OF CHILDREN

In case of accidental overdose, get medical help or contact a Poison Control Center right away. Prompt medical attention is critical for adults as well as for children even if you do not notice any signs or symptoms.

PURPOSE

Cough Suppressant

Expectorant

OTHER SAFETY INFORMATION

* store at room temperature 25°C (77°F) ; excursions permitted between 15°C - 30°C (59°F - 86°F)